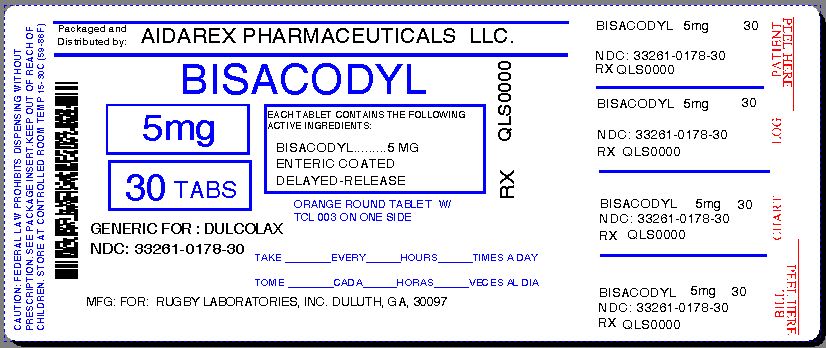 DRUG LABEL: Enteric Coated Stimulant Laxative
NDC: 33261-178 | Form: TABLET, DELAYED RELEASE
Manufacturer: Aidarex Pharmaceuticals LLC
Category: otc | Type: HUMAN OTC DRUG LABEL
Date: 20131213

ACTIVE INGREDIENTS: BISACODYL 5 mg/1 1
INACTIVE INGREDIENTS: ACACIA; CALCIUM SULFATE ANHYDROUS; ANHYDROUS LACTOSE; CARNAUBA WAX; SILICON DIOXIDE; STARCH, CORN; D&C YELLOW NO. 10; FD&C YELLOW NO. 6; GELATIN; FERRIC OXIDE RED; FERROSOFERRIC OXIDE; FERRIC OXIDE YELLOW; MAGNESIUM STEARATE; CELLULOSE, MICROCRYSTALLINE; POLYETHYLENE GLYCOL 400; Polyvinyl Acetate Phthalate; POVIDONES; SHELLAC; SODIUM STARCH GLYCOLATE TYPE A POTATO; STEARIC ACID; SUCROSE; TALC; TITANIUM DIOXIDE

DRUG FACTS

Active ingredient (in each tablet)
Bisacodyl 5 mg

Purpose
Laxative

Uses

- relieves occasional constipation
- generally produces bowel movement in 6-12 hours

Warnings

Do not use

- for longer than one week
- when abdominal pain, nausea or vomiting are present
- in children under 6 years of age
- in persons who cannot swallow without chewing

Ask a doctor before use if you have noticed a sudden change in bowel habits that lasts over two weeks

Ask a doctor or pharmacist before use if you are taking any other drug. Take this product two or more hours before or after other drugs. Laxatives may affect how other drugs work.

When using this product

- do not take dose within one hour of taking an antacid or milk
- you may experience abdominal discomfort, faintness and cramps

Stop use and ask a doctor if

- you have rectal bleeding
- you fail to have a bowel movement after use of this product

These may indicate a serious condition.

PREGNANCY OR BREAST FEEDING

If pregnant or breast-feeding, ask a health professional before use.

Keep out of reach of children. In case of overdose, get medical help or contact a Poison Control Center right away.

Directions
DO NOT CHEW TABLETS
adults and children 12 years and over: 1-3 tablets once daily
children 6 to 11 years: 1 tablet once daily
children under 6 years: ask a doctor

Other information
store at 20°-25°C (68°-77°F)

INACTIVE INGREDIENT

Inactive ingredients acacia, anhydrous calcium sulfate, anhydrous lactose, carnauba wax, colloidal silicon dioxide, corn starch, D-C yellow #10 aluminum lake, FD-C yellow #6 aluminum lake, gelatin, iron oxide, iron oxide black, iron oxide yellow (iron oxide ochre), magnesium stearate, microcrystalline cellulose, polyethylene glycol (PEG) 400, polyvinyl acetate phthalate, povidone, shellac, sodium starch glycolate, stearic acid, sugar, talc, titanium dioxide

Questions or comments?
call 1-800-645-2158 9 am - 5 pm ET, Monday - Friday

Repackaged By :
Aidarex Pharmaceuticals LLC,
Corona, CA 92880